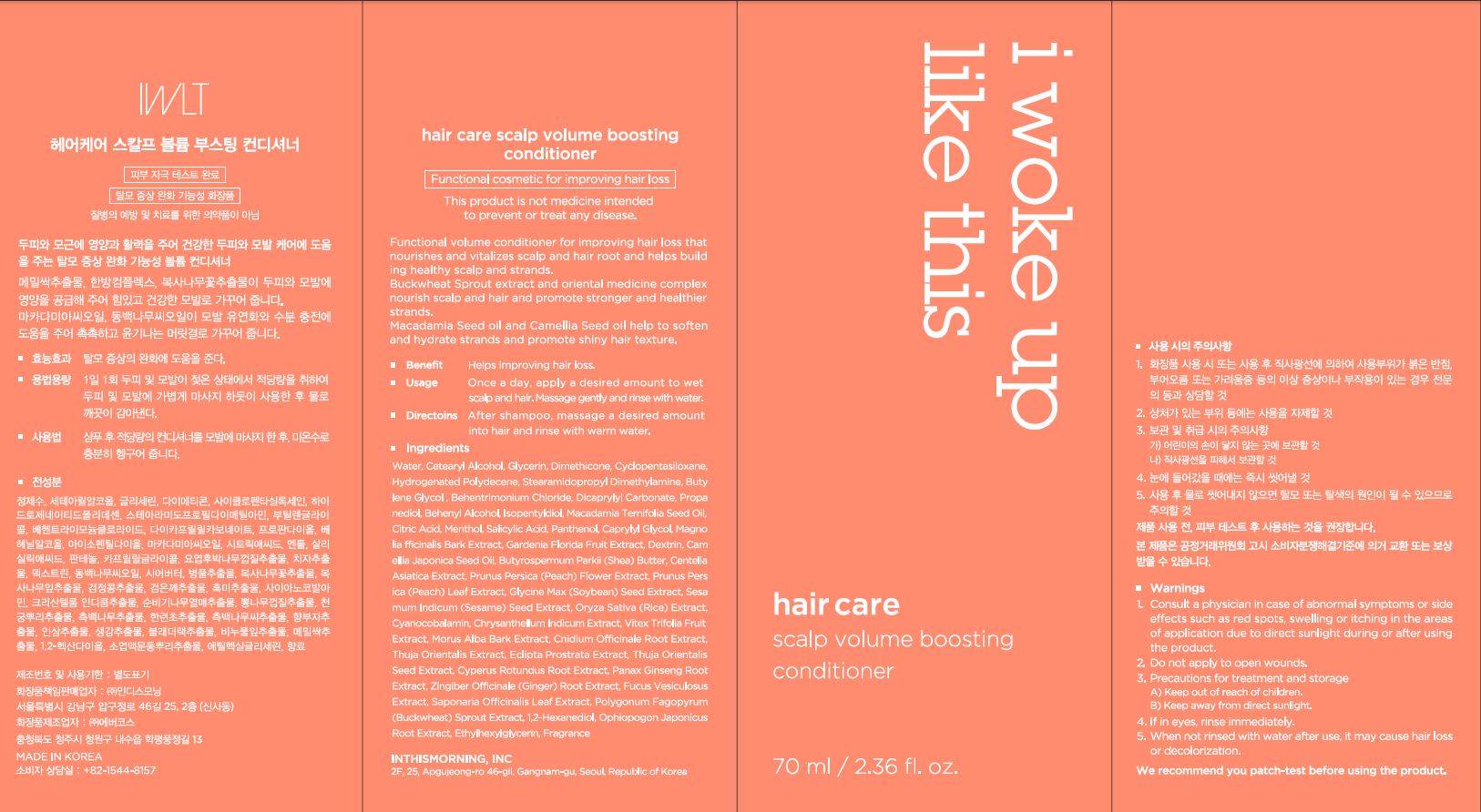 DRUG LABEL: Hair care scalp volume boosting conditioner
NDC: 71217-0068 | Form: LIQUID
Manufacturer: inthismorning co ltd
Category: otc | Type: HUMAN OTC DRUG LABEL
Date: 20230201

ACTIVE INGREDIENTS: BUCKWHEAT 0.0003 g/100 mL
INACTIVE INGREDIENTS: WATER; GLYCERIN

Drug Facts

ACTIVE INGREDIENT

Polygonum Fagopyrum (Buckwheat) Sprout Extract

INACTIVE INGREDIENT

Water
Cetearyl Alcohol
Glycerin
Dimethicone
Cyclopentasiloxane
Hydrogenated Polydecene
Stearamidopropyl Dimethylamine
Butylene Glycol
Behentrimonium Chloride
Dicaprylyl Carbonate
Propanediol
Behenyl Alcohol
Isopentyldiol
Macadamia Ternifolia Seed Oil
Citric Acid
Menthol
Salicylic Acid
Panthenol
Caprylyl Glycol
Magnolia Officinalis Bark Extract
Gardenia Florida Fruit Extract
Dextrin
Camellia Japonica Seed Oil
Butyrospermum Parkii (Shea) Butter
Centella Asiatica Extract
Prunus Persica (Peach) Flower Extract
Prunus Persica (Peach) Leaf Extract
Glycine Max (Soybean) Seed Extract
Sesamum Indicum (Sesame) Seed Extract
Oryza Sativa (Rice) Extract
Cyanocobalamin
Chrysanthellum Indicum Extract
Vitex Trifolia Fruit Extract
Morus Alba Bark Extract
Cnidium Officinale Root Extract
Thuja Orientalis Extract
Eclipta Prostrata Extract
Thuja Orientalis Seed Extract
Cyperus Rotundus Root Extract
Panax Ginseng Root Extract
Zingiber Officinale (Ginger) Root Extract
Fucus Vesiculosus Extract
Saponaria Officinalis Leaf Extract
1,2-Hexanediol
Ophiopogon Japonicus Root Extract
Ethylhexylglycerin
Fragrance

PURPOSE

scalp care

keep out or reach of the children

INDICATIONS AND USAGE

once a day, apply a desired amount to wet scalp and hair,

massage gently and rinse with water

WARNINGS

This product is for exeternal use only. Do not use for internal use
Storage and handling precautions
If possible, avoid direct sunlight and store in cool and area of low humidity in order to maintain the quality of the product and avoid misuse
Avoid placing the product near fire and store out in reach of children

- consult a physician in case of abnormal symptoms, such as red spots, swelling or itching, or side effects in the areas of application due to direct light during or after using the product

- do not use on wounded area

DOSAGE AND ADMINISTRATION

for external use only